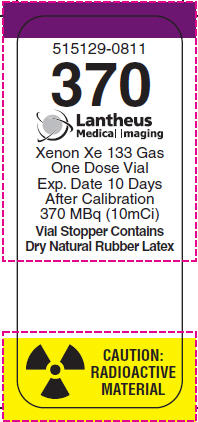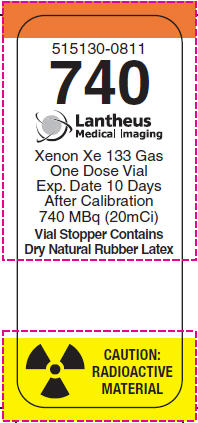 DRUG LABEL: Xenon
NDC: 11994-127 | Form: GAS
Manufacturer: Lantheus Medical Imaging, Inc.
Category: prescription | Type: HUMAN PRESCRIPTION DRUG LABEL
Date: 20221128

ACTIVE INGREDIENTS: XENON XE-133 10 mCi/1 1
INACTIVE INGREDIENTS: CARBON DIOXIDE

XENON Xe 133 GAS
FOR DIAGNOSTIC USE

DESCRIPTION:

Xenon Xe 133 Gas is supplied in a mixture of xenon gas (5%) in carbon dioxide (95%). It is contained within septum sealed glass vials and is suitable for inhalation in the diagnostic evaluation of pulmonary function and imaging, as well as assessment of cerebral blood flow. Xenon Xe 133 Gas is reactor-produced as a by-product of Uranium U235 fission. Each vial contains the labeled amount of Xenon Xe 133 radioactivity at the time of calibration. The contents of the vial are in gaseous form, contain no preservatives, and are ready for use.

Xenon Xe 133 is chemically and physiologically related to elemental Xenon, a non-radioactive monoatomic gas which is physiologically inert except for anesthetic properties at high doses.

PHYSICAL CHARACTERISTICS

Xenon Xe 133 decays by beta and gamma emissions with a half-life of 5.245 days. [Kocher, David C., "Radioactive Decay Data Tables," DOE/TIC-11026, p. 138,1981.] Significant radiations which are emitted by the nuclide are listed in Table 1.

Table 1. Principal Radiation Emission Data from Xenon-133
 | Mean | Mean % per
Radiation | Energy (KeV) | Disintegration
Beta-2 | 100.6 | 99.3
Ce-K-2 | 45.0 | 53.3
Ce-L-2 | 75.3 | 8.1
Ce-M-2 | 79.8 | 1.7
Gamma-2 | 81.0 | 36.5
Kα2X-ray | 30.6 | 13.6
Kα1X-ray | 31.0 | 25.3
KβX-ray | 35.0 | 9.1

EXTERNAL RADIATION

The specific gamma ray constant for Xenon Xe 133 is 3.6 microcoulombs/Kg-MBq-hr (0.51R/hr-mCi) at 1 cm. The first half value thickness of lead is 0.0035 cm. A range of values for the relative attenuation of the radiation emitted by this radionuclide that results from the interposition of various thicknesses of Pb is shown in Table 2. For example, the use of 0.20 cm of Pb will decrease the external radiation exposure by a factor of 1,000.

Table 2. Radiation Attenuation by Lead Shielding
cm of Pb | Radiation Attenuation Factor
0.0035 | 0.5
0.037 | 10^-1
0.12 | 10^-2
0.20 | 10^-3
0.29 | 10^-4

To correct for physical decay of this radionuclide, the fractions that remain at selected time intervals after the time of calibration are shown in Table 3.

Table 3. Xenon Xe 133 Physical Decay Chart (Half Life 5.245 days)
 | Fraction |  | Fraction
Day | Remaining | Day | Remaining
0 [Calibration Day] | 1.000 | 8 | .349
1 | .877 | 9 | .302
2 | .768 | 10 | .268
3 | .674 | 11 | .235
4 | .591 | 12 | .206
5 | .518 | 13 | .181
6 | .452 | 14 | .157
7 | .398

CLINICAL PHARMACOLOGY:

Xenon Xe 133 is a readily diffusible gas which is neither utilized nor produced by the body. It passes through cell membranes and freely exchanges between blood and tissue. It tends to concentrate more in body fat than in blood, plasma, water or protein solutions. In the concentrations used for diagnostic purposes it is physiologically inactive. Inhaled Xenon Xe 133 Gas will enter the alveolar wall and enter the pulmonary venous circulation via the capillaries. Most of the Xenon Xe 133 that enters the circulation from a single breath is returned to the lungs and exhaled after a single pass through the peripheral circulation.

INDICATIONS AND USAGE:

Inhalation of Xenon Xe 133 Gas has proved valuable for the evaluation of pulmonary function and for imaging the lungs. It may also be applied to assessment of cerebral flow.

CONTRAINDICATIONS:

None known.

WARNINGS:

Xenon Xe 133 Gas delivery systems, i.e., respirators or spirometers, and associated tubing assemblies must be leakproof to avoid loss of radioactivity into the environs not specifically protected by exhaust systems.

Xenon Xe 133 adheres to some plastics and rubber and should not be allowed to stand in tubing or respirator containers. The unrecognized loss of radioactivity from the dose for administration may render the study non-diagnostic.

The vial stopper contains dry natural rubber latex and may cause allergic reactions in providers or patients who are sensitive to latex.

PRECAUTIONS:

General

Xenon Xe 133, as well as other radioactive drugs, must be handled with care and appropriate safety measures should be used to minimize radiation exposure to clinical personnel. Also, care should be taken to minimize radiation exposure to patients consistent with proper patient management.

Exhaled Xenon Xe 133 Gas should be controlled in a manner that is in compliance with the appropriate regulations of the government agency authorized to license the use of radionuclides.

Radiopharmaceuticals should be used only by physicians who are qualified by training and experience in the safe use and handling of radionuclides and whose experience and training have been approved by the appropriate government agency authorized to license the use of radionuclides.

Carcinogenesis, Mutagenesis, Impairment of Fertility

No long term animal studies have been performed to evaluate carcinogenic potential or whether Xenon Xe 133 affects fertility in males or females.

Pregnancy

Animal reproductive studies have not been conducted with Xenon Xe 133 Gas. It is also not known whether Xenon Xe 133 Gas can cause fetal harm when administered to a pregnant woman or can affect reproduction capacity. Xenon Xe 133 Gas should be given to a pregnant woman only if clearly needed.

Ideally, examination using radiopharmaceuticals, especially those elective in nature in a woman of childbearing capability, should be performed during the first few (approximately 10) days following the onset of menses.

Nursing Mothers

It is not known whether Xenon Xe 133 is excreted in human milk. Many drugs are excreted in human milk, therefore formula feedings should be substituted for breast feeding, because of the potential for adverse reactions in nursing infants.

Pediatric Use

Safety and effectiveness in the pediatric population has not been established.

Geriatric Use

Clinical studies of Xenon Xe 133 Gas did not include sufficient numbers of subjects aged 65 and over to determine whether they respond differently from younger subjects. Other reported clinical experience has not identified differences in responses between the elderly and younger patients. In general, dose selection for an elderly patient should be cautious, usually starting at the low end of the dosage range, reflecting the greater frequency of decreased hepatic, renal, or cardiac function, and of concomitant disease or other drug therapy.

ADVERSE REACTIONS:

Adverse reactions related to the use of this agent have not been reported to date.

DOSAGE AND ADMINISTRATION:

Xenon Xe 133 Gas is administered by inhalation from closed respirator systems or spirometers.

The suggested activity range employed for inhalation by the average adult patient (70 kg) is:

Pulmonary function including imaging: 74-1110MBq (2-30mCi) in 3 liters of air.

Cerebral blood flow: 370-1110MBq (10-30mCi) in 3 liters of air.

The patient dose should be measured by a suitable radioactivity calibration system immediately prior to administration.

RADIATION DOSIMETRY

The estimated absorbed radiation doses [Method of Calculation: A Schema for Absorbed-Dose Calculation for Biologically Distributed Radionuclides, Supplement No. 1, MIRD pamphlet No. 1, J. Nucl. Med., p.7 (1968).] to an average patient (70 kg) for pulmonary perfusion and cerebral blood flow studies from a maximum dose of 1110 MBq (30mCi) of Xenon Xe 133 in 3 liters of air are shown in Table 4.

Table 4. Radiation Doses
 | Effective |  |  | Whole
 | Half-Time | Lungs [99% of activity is in lungs.] | Brain | Body
 |  |  | mGy/1110MBq | (rads/30mCi)
Pulmonary Perfusion | 2 min. | 2.5(0.25) | 0.014(0.0014) | 0.027(0.0027)
Cerebral Blood Flow | 5 min. | 6.3(0.63) | 0.035(0.0035) | 0.068(0.0068)

HOW SUPPLIED:

The Xenon Xe 133 Gas is supplied as part of the Calidose™ system, consisting of 3ml unit dose vials and the Calidose™ dispenser for shielded dispensing.

Normally vials containing either 370 or 740MBq (10 or 20mCi)/vial, packed 1 vial or 5 vials per shield tube, are supplied.

The NDC number for: 10mCi vial is 11994-127; 20mCi vial is 11994-128.

Store at room temperature.

This radiopharmaceutical is approved for distribution to persons licensed pursuant to the Code of Massachusetts Regulations 105 CMR 120.100 for the uses listed in 105 CMR 120. 547 or 120.552 or under equivalent regulations of the U.S. Nuclear Regulatory Commission, an Agreement State, or a Licensing State.

The contents of the vial are radioactive. Adequate shielding and handling precautions must be maintained.

Lantheus Medical Imaging, Inc.

331 Treble Cove Rd., N. Billerica, MA 01862 USA
For Ordering Tel. Toll Free 800-299-3431
(For Massachusetts & International, Call 978-667-9531)
All Other Business 800-362-2668
Patent: http://www.lantheus.com/patents/index.html

Printed in U.S.A.

515083-0719
July 2019

PRINCIPAL DISPLAY PANEL - 10mCi Vial Label

515129-0811

370

Lantheus
Medical Imaging

Xenon Xe 133 Gas
One Dose Vial
Exp. Date 10 Days
After Calibration
370 MBq (10mCi)

Vial Stopper Contains
Dry Natural Rubber Latex

CAUTION:
RADIOACTIVE
MATERIAL

PRINCIPAL DISPLAY PANEL - 20mCi Vial Label

515130-0811

740

Lantheus
Medical Imaging

Xenon Xe 133 Gas
One Dose Vial
Exp. Date 10 Days
After Calibration
740 MBq (20mCi)

Vial Stopper Contains
Dry Natural Rubber Latex

CAUTION:
RADIOACTIVE
MATERIAL